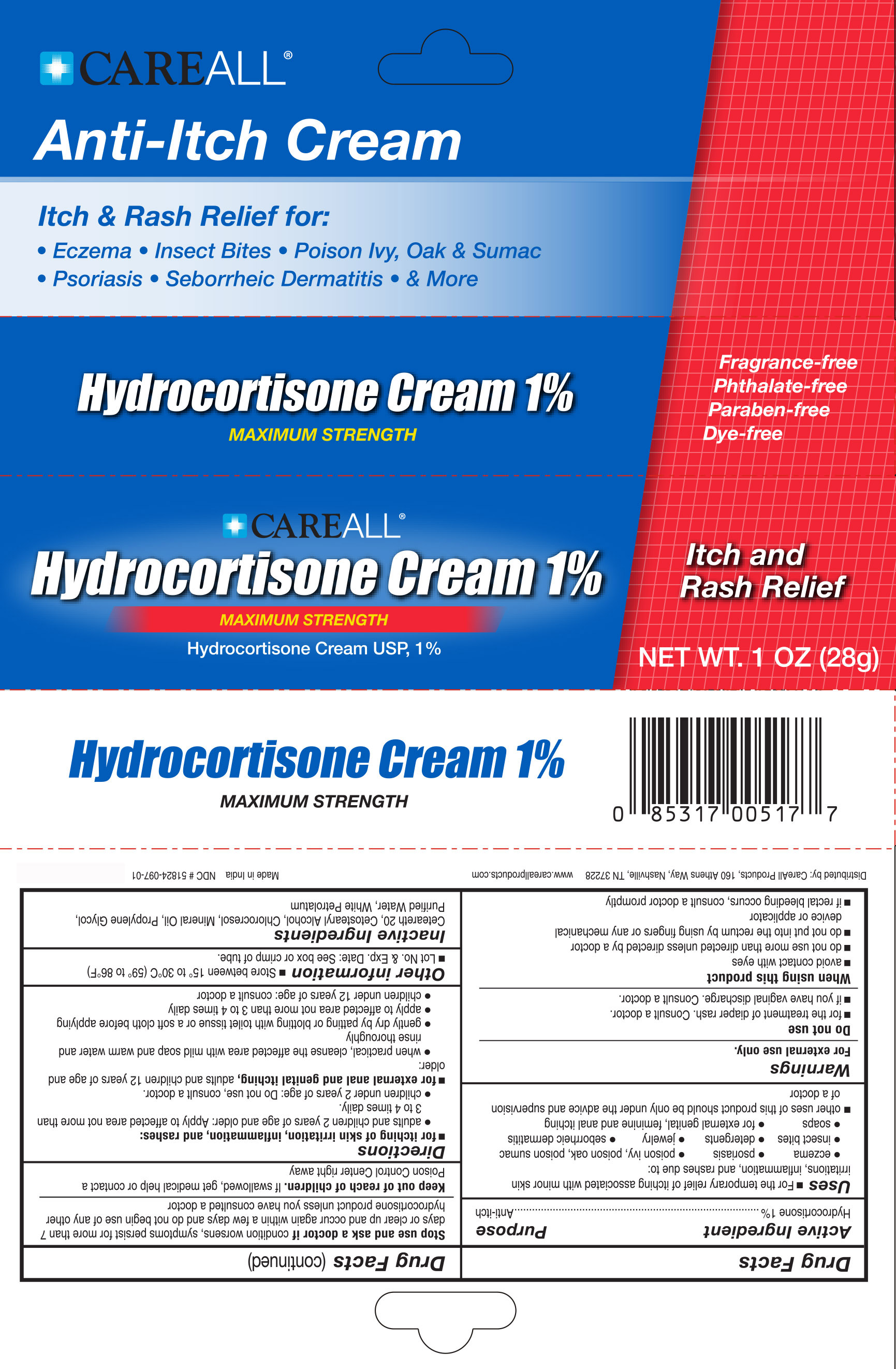 DRUG LABEL: CAREALL Hydrocortisone 

NDC: 51824-097 | Form: CREAM
Manufacturer: New World Imports, Inc
Category: otc | Type: HUMAN OTC DRUG LABEL
Date: 20251201

ACTIVE INGREDIENTS: HYDROCORTISONE 0.01 g/1 g
INACTIVE INGREDIENTS: PROPYLENE GLYCOL; WHITE PETROLATUM; MINERAL OIL; CETOSTEARYL ALCOHOL; POLYOXYL 20 CETOSTEARYL ETHER; CHLOROCRESOL; WATER

Drug Facts

Active Ingredient

Hydrocortisone 1%

Purpose

Anti-Itch

Keep out of reach of children. If swallowed, get medical help or contact a Poison Control Center right away

Uses

- For the temporary relief of itching associated with minor skin irritations, inflammation, and rashes due to: eczema, psoriasis, poison ivy, oak & sumac, insect bites, detergents, jewelry, seborrheic dermatitis, soap as well as for external genital, geminine and anal itching
- Other uses of this product should be only under the advice and supervision of a doctor

Warnings

For external use only

Do not use:

For the treatment of diaper rash. Consult a doctor

if you have vaginal discharge. Consult a doctor

When using this product:

Avoid contact with the eyes

Do not use more than directed unless told to do so by a doctor.

Do not put this product into the rectum by using fingers or any mechanical device or applicator

If rectal bleeding occurs, consult a doctor promptly

Stop use and ask a doctor if:

Condition worsens, symptoms persist for more than 7 days or clear up and occur again within a few days and do not begin use of any other hydrocortisone product unless you have asked a doctor.

Directions

for itching of skin irritation, inflammation and rashes:

- Adults and children 2 years of age and older: apply to affected area not more than 3 to 4 times daily.
- Children under 2 years of age do not use. Ask a doctor.

For external anal and genital itching,adults and children 12 years of age and older:

- when practical, cleanse the affected area with mild soap and warm water and rinse thoroughly.
- Gently dry by patting or blotting with toliet tissue or a soft cloth before applying.
- apply to affected area not more than 3 to 4 times daily.
- children under 12 years of age with external anal itching: consult a doctor.

INACTIVE INGREDIENT

Ceteareth 20, Cetostearyl Alcohol, Chlorocresol, Mineral Oil, Propylene Glycol, Purified Water, White Petrolatum